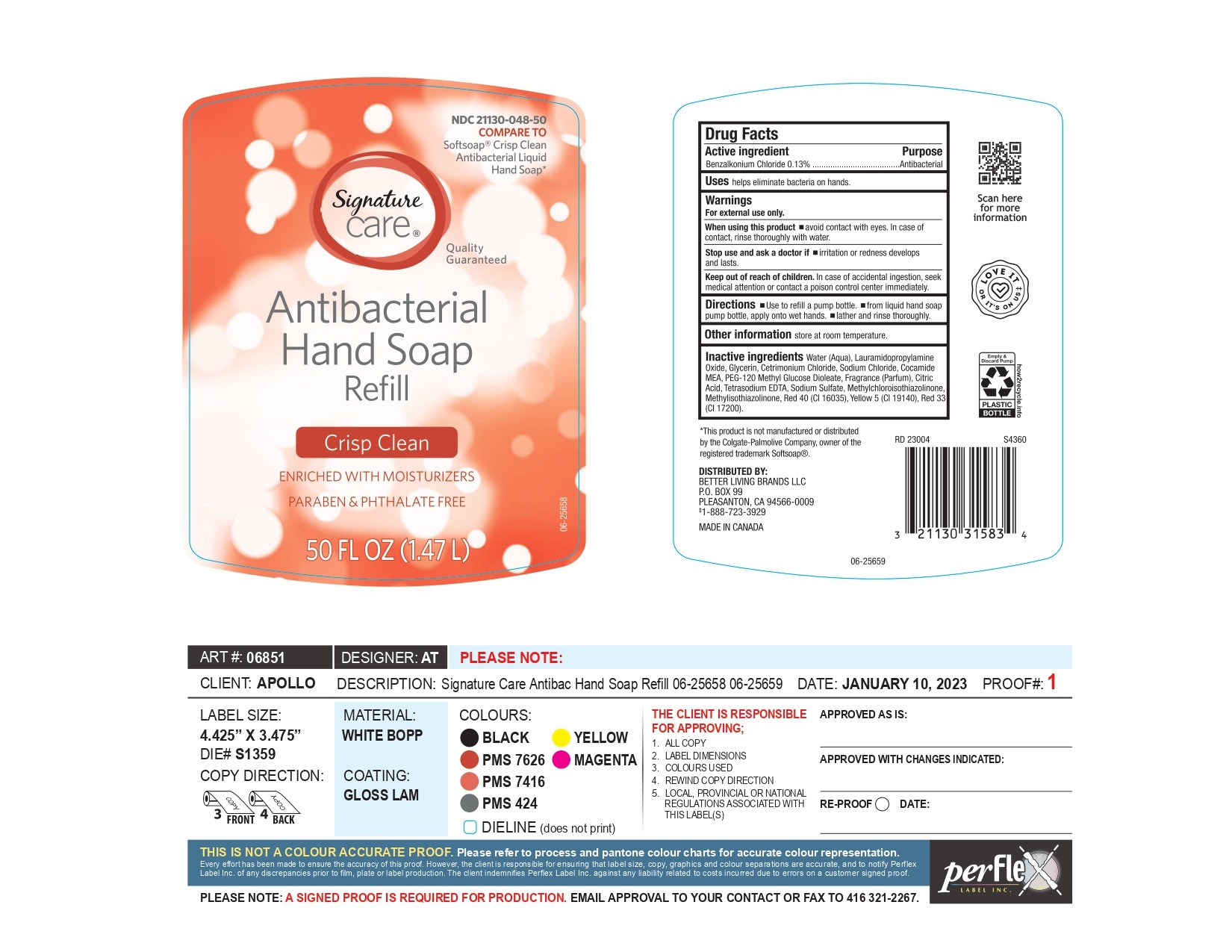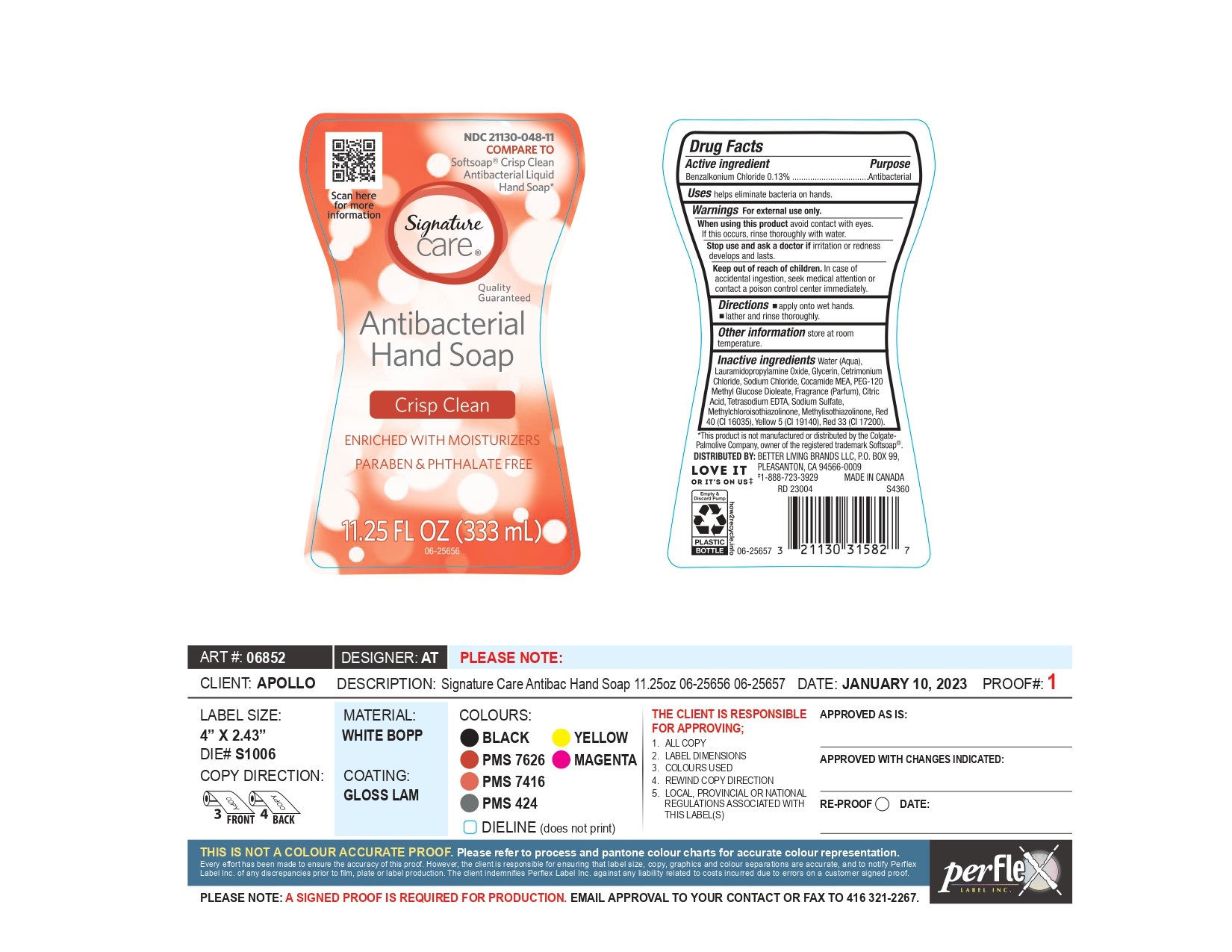 DRUG LABEL: Better Living Brands
NDC: 21130-048 | Form: SOAP
Manufacturer: Better Living Brands LLC
Category: otc | Type: HUMAN OTC DRUG LABEL
Date: 20250206

ACTIVE INGREDIENTS: BENZALKONIUM CHLORIDE 130 mg/100 mL
INACTIVE INGREDIENTS: RED 33; CITRIC ACID; EDETATE SODIUM; WATER; LAURAMIDOPROPYLAMINE OXIDE; SODIUM CHLORIDE; GLYCERIN; SODIUM SULFATE; METHYLCHLOROISOTHIAZOLINONE; CETRIMONIUM CHLORIDE; METHYLISOTHIAZOLINONE; PEG-120 METHYL GLUCOSE DIOLEATE; FD&C RED NO. 40; BASIC YELLOW 5; FRAGRANCE CLEAN ORC0600327; COCAMIDE MEA

Better Living Brands- NDC-21130-048

ACTIVE INGREDIENT

Benzalkonium chloride 0.13%

PURPOSE

Antibacterial

INDICATIONS AND USAGE

helps eliminate bacteria on hands

WARNINGS

For external use only

WHEN USING

Avoid contact with eyes. If contact occurs, rinse eyes thoroughly with water.

Ask a doctor

if irritation or redness develops and lasts

KEEP OUT OF REACH OF CHILDREN

incase of accidental ingestion, seek medical attention or contact a poison control centre immediately.

Directions

- Apply onto wet hands.
- lather and rinse thoroughly

STORAGE AND HANDLING

Store at room temperature

INACTIVE INGREDIENT

Water, Lauramidopropylamine oxide, Glycerin, Cetrimonium Chloride, Sodium chloride, Cocamide MEA , PEG-120 Methyl Glucose Dioleate, fragrance, Citric Acid , Tetrasodium EDTA, Sodium sulfate, Methylchloroisothiazolinone, Methylisothiazolinone, Red 40, Yellow 5, Red 33

QUESTIONS

1-888-723-3929